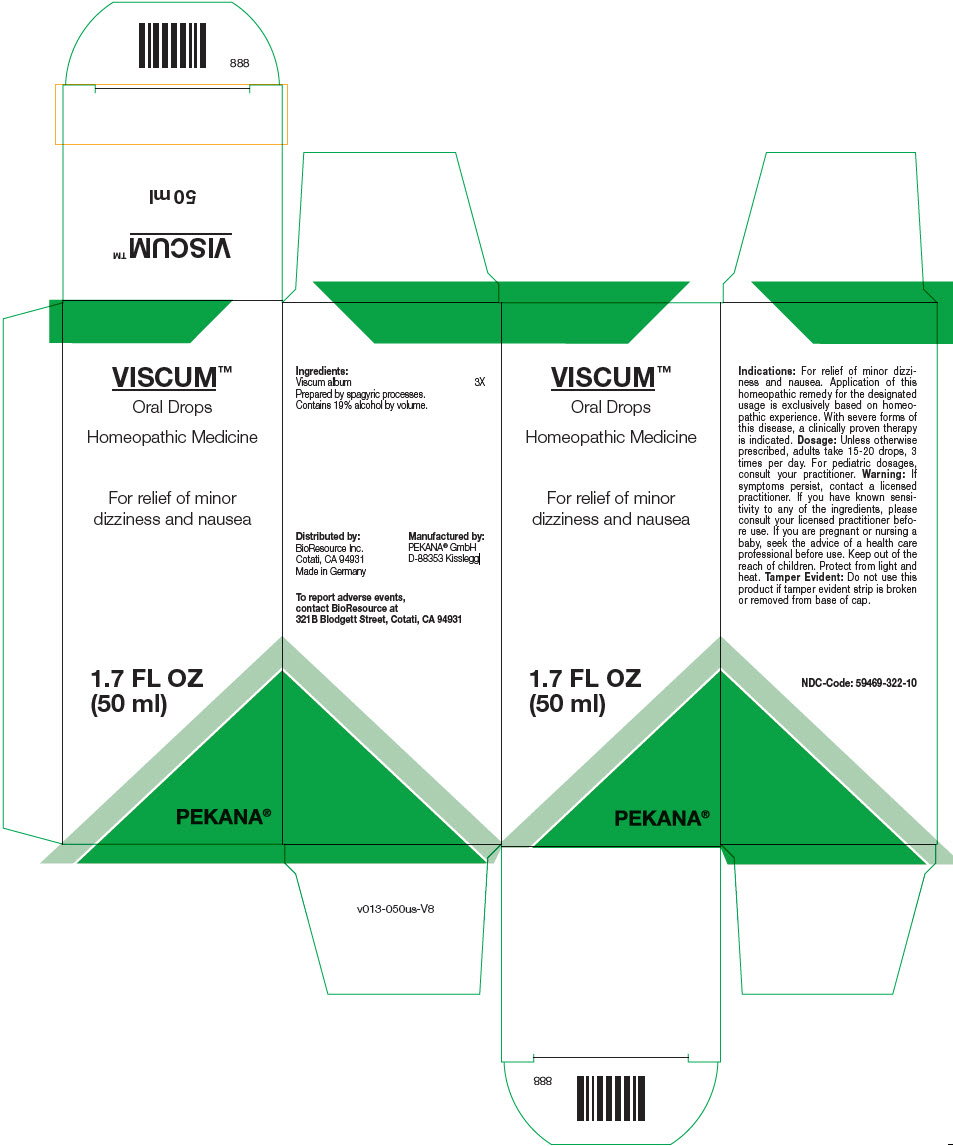 DRUG LABEL: VISCUM
NDC: 59469-322 | Form: SOLUTION/ DROPS
Manufacturer: PEKANA Natuheilmittel GmbH
Category: homeopathic | Type: HUMAN OTC DRUG LABEL
Date: 20230111

ACTIVE INGREDIENTS: VISCUM ALBUM FRUITING TOP 3 [hp_X]/50 mL
INACTIVE INGREDIENTS: WATER; ALCOHOL

VISCUM™

ACTIVE INGREDIENT

Ingredients:
Viscum album | 3X

Prepared by spagyric processes.

INACTIVE INGREDIENT

Contains 19% alcohol by volume.

Indications

PURPOSE

For relief of minor dizziness and nausea. Application of this homeopathic remedy for the designated usage is exclusively based on homeopathic experience. With severe forms of this disease, a clinically proven therapy is indicated.

Dosage

Unless otherwise prescribed, adults take 15-20 drops, 3 times per day. For pediatric dosages, consult your practitioner.

Warning

ASK DOCTOR

If symptoms persist, contact a licensed practitioner. If you have known sensitivity to any of the ingredients, please consult your licensed practitioner before use. If you are pregnant or nursing a baby, seek the advice of a health care professional before use.

Keep out of the reach of children.

STORAGE AND HANDLING

Protect from light and heat.

Tamper Evident

Do not use this product if tamper evident strip is broken or removed from base of cap.

QUESTIONS

To report adverse events, contact BioResource at 321B Blodgett Street, Cotati, CA 94931

Distributed by:
BioResource Inc.
Cotati, CA 94931

Manufactured by:
PEKANA® GmbH
D-88353 Kisslegg

PRINCIPAL DISPLAY PANEL - 50 ml Bottle Box

VISCUM™

Oral Drops

Homeopathic Medicine

For relief of minor
dizziness and nausea

1.7 FL OZ
(50 ml)

PEKANA®